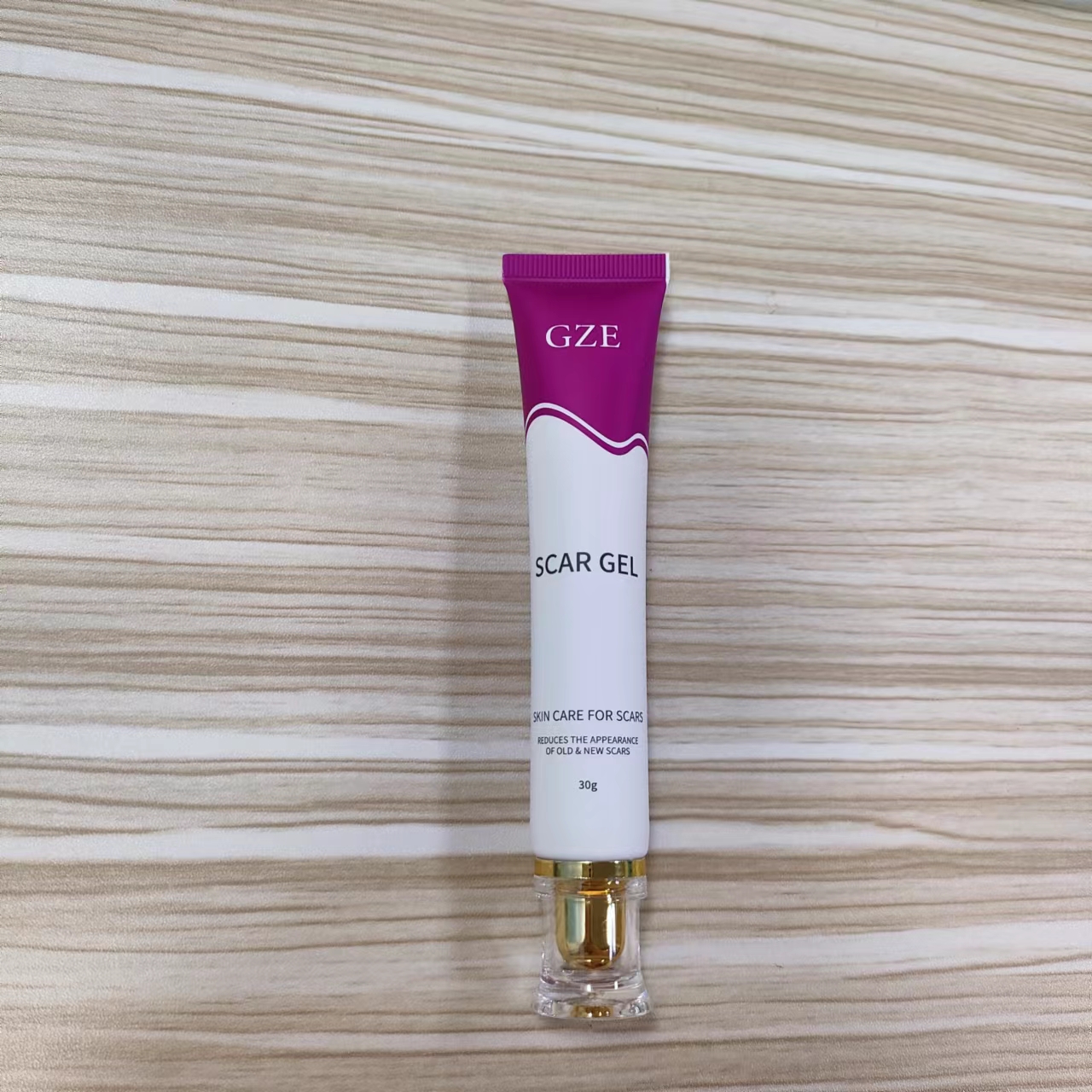 DRUG LABEL: GZE Scar Gel
NDC: 74458-027 | Form: GEL
Manufacturer: Guangzhou Yilong Cosmetics Co., Ltd
Category: otc | Type: HUMAN OTC DRUG LABEL
Date: 20241024

ACTIVE INGREDIENTS: ALLANTOIN 0.5 g/100 g
INACTIVE INGREDIENTS: LECITHIN, SOYBEAN; SODIUM HYALURONATE; ALCOHOL; PANTHENOL; WATER; ALLIUM CEPA (ONION) BULB EXTRACT; SORBIC ACID; POLYETHYLENE GLYCOL 200; XANTHAN GUM; METHYLPARABEN; FRAGRANCE 13576

GZE SCAR GEL

ACTIVE INGREDIENT

Allantoin 0.5%

INACTIVE INGREDIENT

Water (purified)

PEG 200

Alcohol

Xanthan Gum

Lecithin

Methylparaben

Sorbic Acid

Panthenol

Sodium Hyaluronate

Fragrance

INDICATIONS AND USAGE

Apply evenly and gently rub into the scar once a day for 8 weeks on new sars, and once a day for 3-6 months on existing scars.Apply Scar Gel as soon as your wound has closed.

PURPOSE

Skin care for scar.

WARNINGS

For external use only.

Stop use and ask a doctor if rash occurs.

Do not use on damaged or broken skin.

Keep out of reach of children. If swallowed, get medical help or contact a Poison Control Center right away.

DOSAGE AND ADMINISTRATION

Apply evenly and gently rub into the scar once a day for 8 weeks on new sars, and once a day for 3-6 months on existing scars.Apply Scar Gel as soon as your wound has closed.